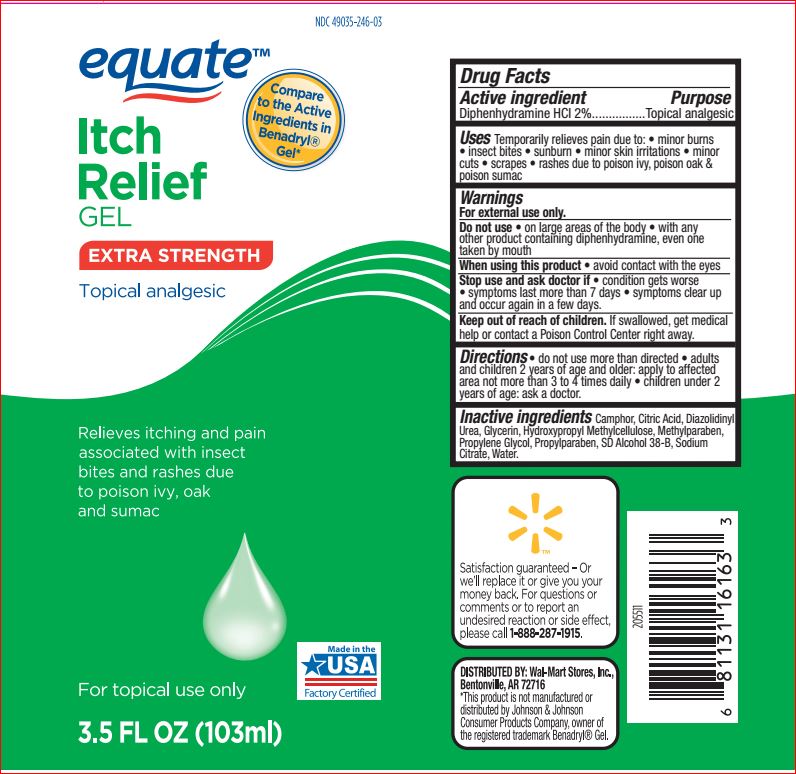 DRUG LABEL: Each Relief
NDC: 49035-246 | Form: GEL
Manufacturer: Walmart
Category: otc | Type: HUMAN OTC DRUG LABEL
Date: 20170120

ACTIVE INGREDIENTS: DIPHENHYDRAMINE HYDROCHLORIDE 2 g/100 mL
INACTIVE INGREDIENTS: CAMPHOR (SYNTHETIC); CITRIC ACID MONOHYDRATE; Diazolidinyl Urea; Glycerin; HYPROMELLOSE, UNSPECIFIED; Methylparaben; Propylene Glycol; Propylparaben; ALCOHOL; Sodium Citrate; Water

Drug Facts

Active ingredient Purpose
Diphenhydramine HCI 2%................Topical analgesic

INDICATIONS AND USAGE

Uses Temporarily relieves pain due to: • minor burns • insect bites • sunburn • minor skin irritations • minor cuts • scrapes • rashes due to poison ivy, poison oak & poison sumac

Warnings
For external use only.
Do not use • on large areas of the body • with any other product containing diphenhydramine, even one taken by mouth
When using this product • avoid contact with the eyes
Stop use and ask doctor if • condition gets worse • symptoms last more than 7 days • symptoms clear up and occur again in a few days.

Keep out of reach of children. If swallowed, get medical help or contact a Poison Control Center right away.

DOSAGE AND ADMINISTRATION

Directions • do not use more than directed • adults and children 2 years of age and older: apply to affected area not more than 3 to 4 times daily • children under 2 years of age: ask a doctor.

Inactive ingredients

Camphor, Citric Acid, Diazolidinyl
Urea, Glycerin, Hydroxypropyl Methylcellulose, Methylparaben,
Propylene Glycol, Propylparaben, SD Alcohol 38-B, Sodium
Citrate, Water.